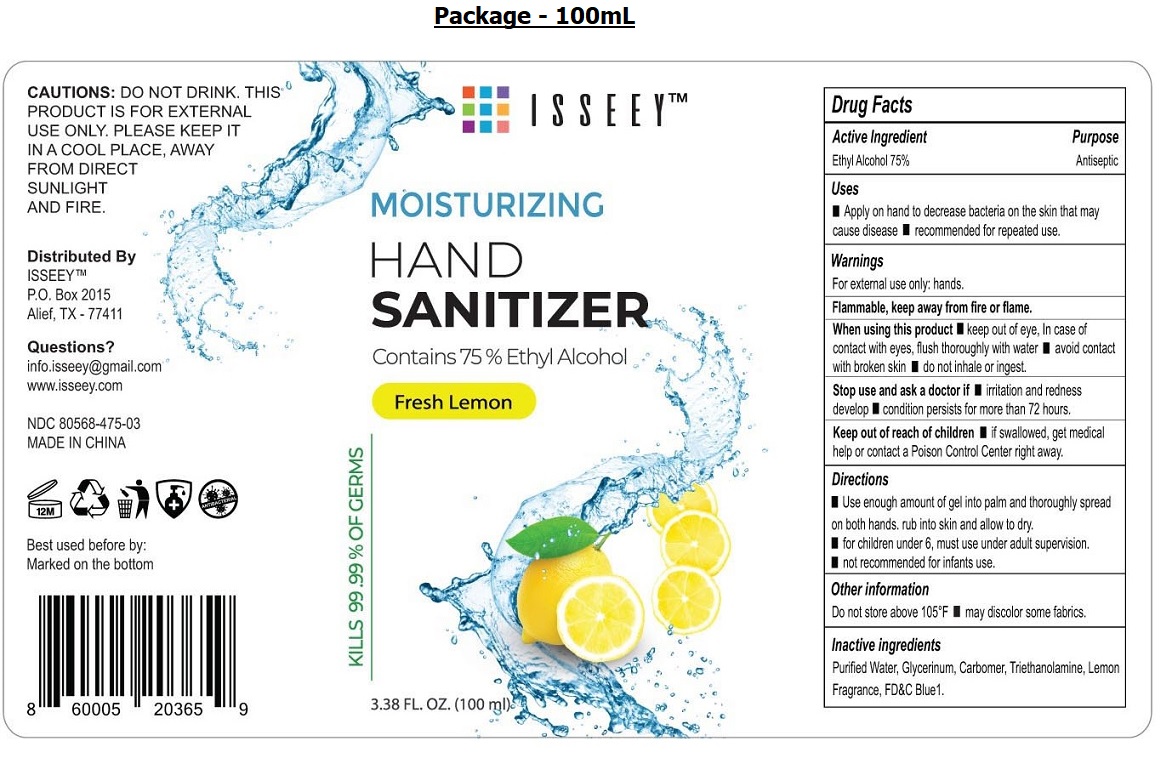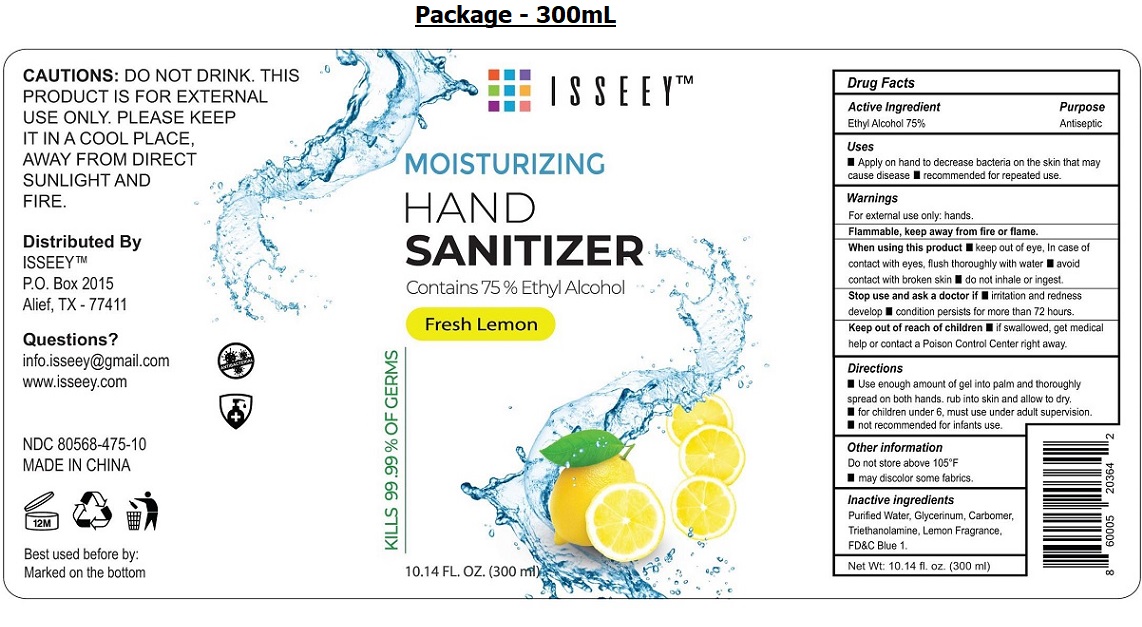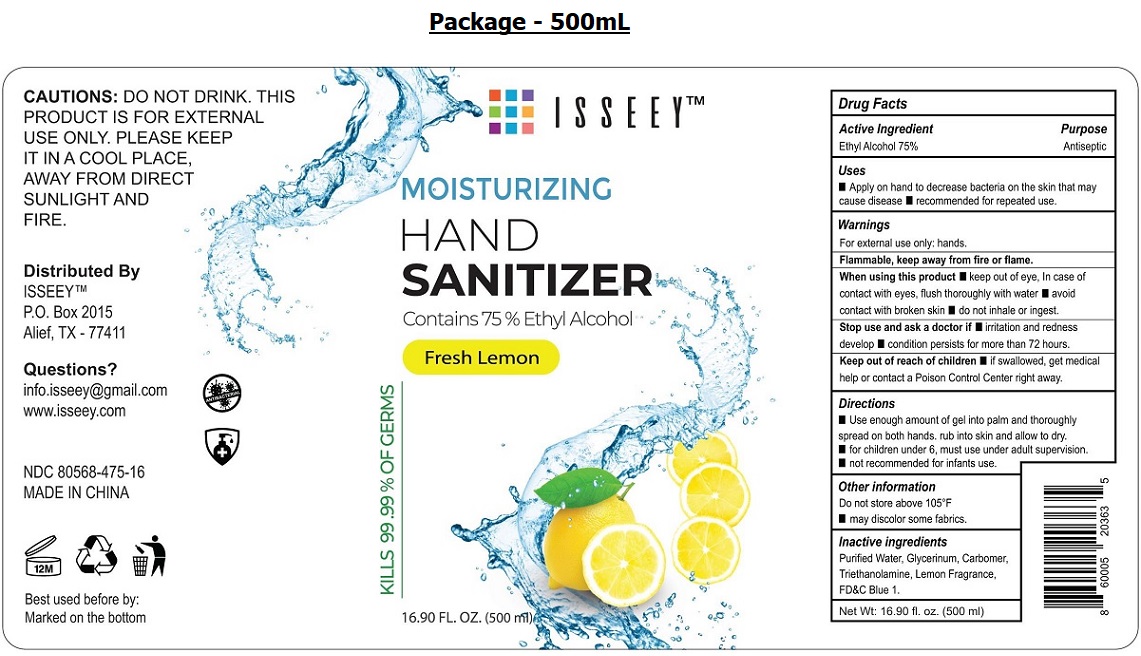 DRUG LABEL: ISSEEY - MOISTURIZING HAND SANITIZER - LEMON
NDC: 80568-475 | Form: GEL
Manufacturer: ISSEEY
Category: otc | Type: HUMAN OTC DRUG LABEL
Date: 20200917

ACTIVE INGREDIENTS: ALCOHOL 75 mL/100 mL
INACTIVE INGREDIENTS: WATER; GLYCERIN; CARBOMER HOMOPOLYMER, UNSPECIFIED TYPE; TROLAMINE; LEMON OIL; FD&C BLUE NO. 1

ISSEEY TM- MOISTURIZING HAND SANITIZER - LEMON

Active Ingredient

Ethyl Alcohol 75%

Purpose

Antiseptic

Uses

■ Apply on hand to decrease bacteria on the skin that may cause disease ■ recommended for repeated use.

Warnings

For external use only: hands.

Flammable, keep away from fire or flame.

When using this product ■ keep out of eye, In case of contact with eyes, flush thoroughly with water ■ avoid contact with broken skin ■ do not

inhale or ingest.

Stop use and ask a doctor if ■ irritation and redness develop ■ condition persists for more than 72 hours.

Keep out of reach of children. ■ if swallowed, get medical help or contact a Poison Control Center right away.

Directions

■ Use enough amount of gel into palm and thoroughly spread on both hands. rub into skin and allow to dry.

■ for children under 6, must use under adult supervision.

■ not recommended for infants use.

Other information

Do not store above 105°F

■ may discolor some fabrics.

Inactive ingredients

Purified Water, Glycerinum, Carbomer, Triethanolamine, Lemon Fragrance, FD&C Blue1.

Fresh Lemon

KILLS 99.99% OF GERMS

CAUTIONS: DO NOT DRINK. THIS PRODUCT IS FOR EXTERNAL USE ONLY. PLEASE KEEP IT IN A COOL PLACE, AWAY FROM DIRECT

SUNLIGHT AND FIRE

Distributed By

ISSEEY TM

P.O. Box 2015

Alief, TX - 77411

Questions?

info.isseey@gmail.com

www.isseey.com

MADE IN CHINA

Best used before by:

Marked on the bottom